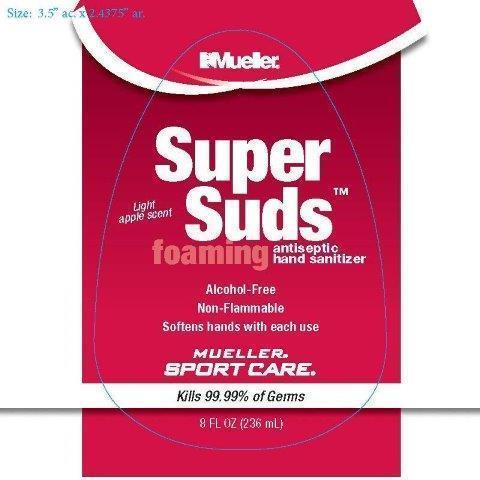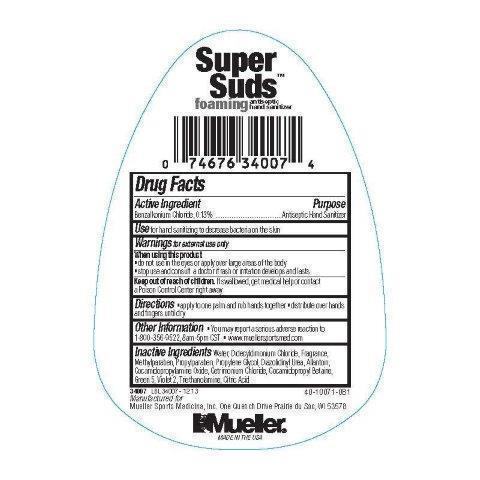 DRUG LABEL: Mueller Super Suds
NDC: 52564-340 | Form: LOTION
Manufacturer: Mueller Sports Medicine, Inc.
Category: otc | Type: HUMAN OTC DRUG LABEL
Date: 20141124

ACTIVE INGREDIENTS: BENZALKONIUM CHLORIDE 0.13 mg/1 mL
INACTIVE INGREDIENTS: Water; COCAMIDOPROPYL BETAINE; CETRIMONIUM CHLORIDE; COCAMIDOPROPYLAMINE OXIDE; DIDECYLDIMONIUM CHLORIDE; METHYLPARABEN; PROPYLPARABEN; PROPYLENE GLYCOL; DIAZOLIDINYL UREA; ALLANTOIN; TROLAMINE; CITRIC ACID MONOHYDRATE

PACKAGE LABEL

ACTIVE INGREDIENT

Benzalkonium Chloride, 0.13%

PURPOSE

Antiseptic Hand Sanitizer

KEEP OUT OF REACH OF CHILDREN

Keep out of reach if children. If swallowed, get medical help or contact a Poison Center right away.

INDICATIONS AND USAGE

Use for hand sanitizing to decrease bacteria on the skin.

WARNINGS

For external use only.

Do not use in the eyes or apply over large areas of the baody. Stop use and consult a doctor if rash or irritation develops or lasts.

DOSAGE AND ADMINISTRATION

Directions. Apply to one palm and rub hands together. Distribute over hands and fingers until dry.

You may report a serious adverse reaction to 1-800-356-9522, 8am - 5pm CST. www.muellersportsmedicine.com

INACTIVE INGREDIENT

Water, Didecyldimonium Chloride , Fragrance, Methylparaben, Propylparaben, Propylene Glycol, Diazolidinyl Urea, Allantoin, Cocamidopropylamine Oxide, Cetrimonium Chloride, Cocamidopropyl Betaine, Green 5, Violet 2, Triethanolamine, Citric Acid.